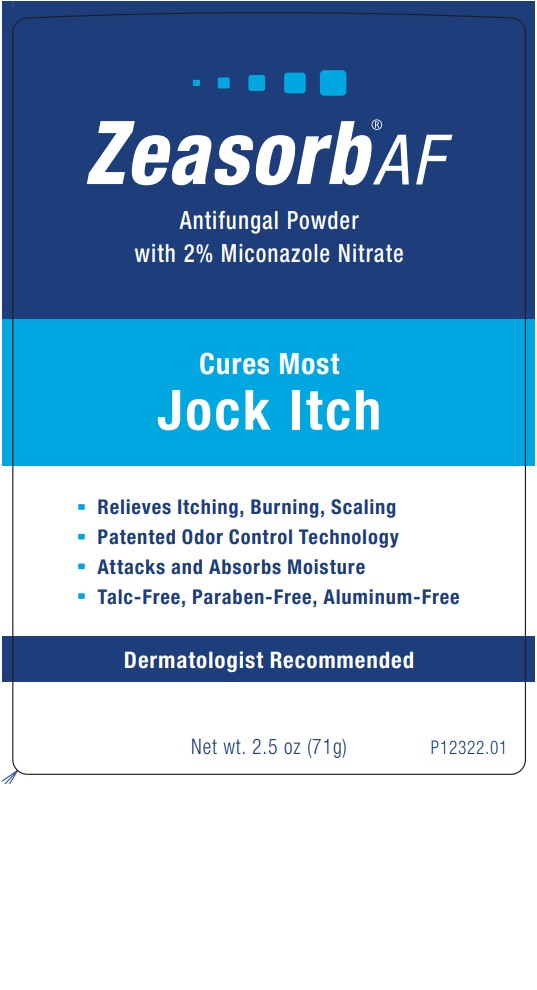 DRUG LABEL: Zeasorb Jock Itch
NDC: 0316-8001 | Form: POWDER
Manufacturer: Crown Laboratories
Category: otc | Type: HUMAN OTC DRUG LABEL
Date: 20260112

ACTIVE INGREDIENTS: MICONAZOLE NITRATE 20 mg/1 g
INACTIVE INGREDIENTS: ALOE VERA LEAF; POTASSIUM SORBATE; SODIUM BENZOATE; STARCH, TAPIOCA; TRICALCIUM PHOSPHATE; WATER; STARCH, CORN; BENTONITE

Zeasorb Jock Itch

Active ingredient

Miconazole nitrate 2%

Purpose

Antifungal

Use

- Proven clinically effective in the treament of most jock itch

Warnings

For external use only.

Avoid contact with the eyes.

Do not use

on children under 2 years of age unless directed by a doctor.

If irritation occurs or if there is no improvement within 2 weeks, discontinue use and consult a doctor.

Keep out of reach of children.

If swallowed, get medical help or contact a poison control center right away.

Directions

Wash the affected area and dry thoroughly. Apply a thin layer of the product over affected area twice daily (morning and night) or as directed by a doctor. Supervise children in the use of this product. Use daily for 2 weeks. If condition persists longer, consult a doctor. This product is not effective on the scalp or nails.

Other information

- store at 20o - 25oC (68o - 77oF) [see USP Controlled Room Temperature]. Product settles during shipment. Package contains full net weight.

Inactive ingredients

Aloe Barbadensis Leaf Juice Powder, Bentonite, Fragrance, Potassium Sorbate, Sodium Benzoate, Tapioca Starch, Tricalcium Phosphate, Water, Zea Mays (Corn) Starch

Questions?

call 1-833-279-6522

Principal Display

Zeasorb®AF

Antifungal Powder

with 2% Miconazole Nitrate

Cures Most Jock Itch

Relieves Itching, Burning, Scaling

Patented Odor Control Technology

Attacks and Absorbs Moisture

Talc-Free, Paraben-Free, Aluminum-Free

Dermatologist Recommended

Net wt. 2.5 oz (71g)

P12322.01